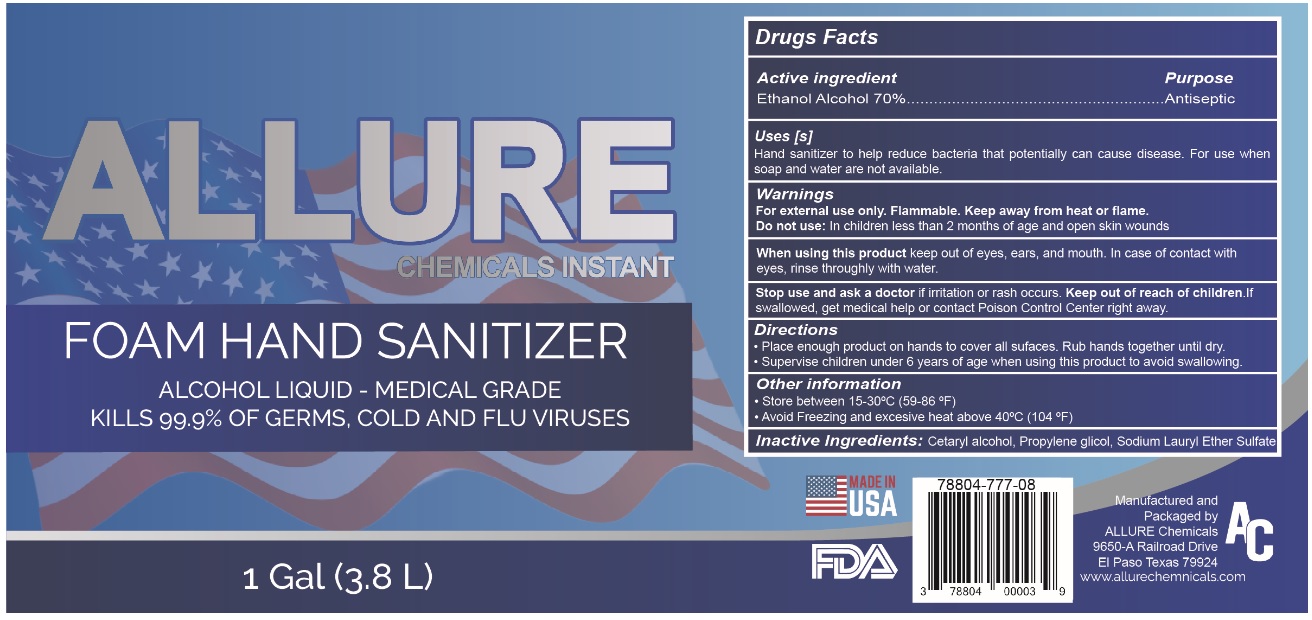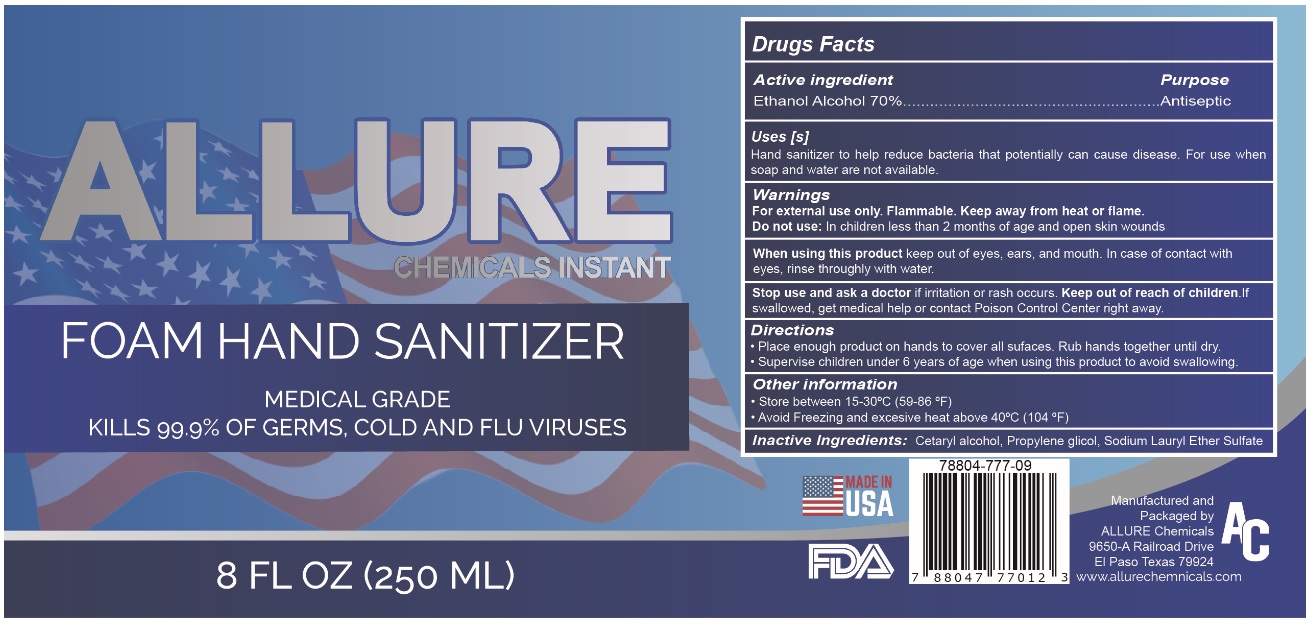 DRUG LABEL: Allure Chemicals Instant Foam Hand Sanitizer
NDC: 78804-777 | Form: LIQUID
Manufacturer: Allure Chemicals LP
Category: otc | Type: HUMAN OTC DRUG LABEL
Date: 20201013

ACTIVE INGREDIENTS: ALCOHOL 70 mL/100 mL
INACTIVE INGREDIENTS: CETOSTEARYL ALCOHOL; PROPYLENE GLYCOL; SODIUM LAURETH-3 SULFATE

ALLURE CHEMICALS INSTANT FOAM HAND SANITIZER

Active ingredient

Ethanol Alcohol 70%

Purpose

Antiseptic

Uses [s]

Hand sanitizer to help reduce bacteria that potentially can cause disease. For use when soap and water are not available.

Warnings

For external use only. Flammable. Keep away from heat or flame.

Do not use: In children less than 2 months of age and open skin wounds

When using this product keep out of eyes, ears, and mouth. In case of contact with eyes, rinse thoroughly with water.

Stop use and ask a doctor if irritation or rash occurs.

Keep out of reach of children. If swallowed, get medical help or contact Poison Control Center right away.

Directions

• Place enough product on hands to cover all surfaces. Rub hands together until dry.

• Supervise children under 6 years of age when using this product to avoid swallowing.

Other information

• Store between 15-30°C (59-86°F)

• Avoid Freezing and excessive heat above 40°C (104°F)

Inactive Ingredients:

Cetaryl alcohol, Propylene glycol, Sodium Lauryl Ether Sulfate

ALCOHOL LIQUID - MEDICAL GRADE

KILLS 99.9% OF GERMS, COLD AND FLU VIRUSES

Manufactured and Packaged by

ALLURE Chemicals

9650-A Railroad Drive

El Paso Texas 79924

www.allurechemicals.com